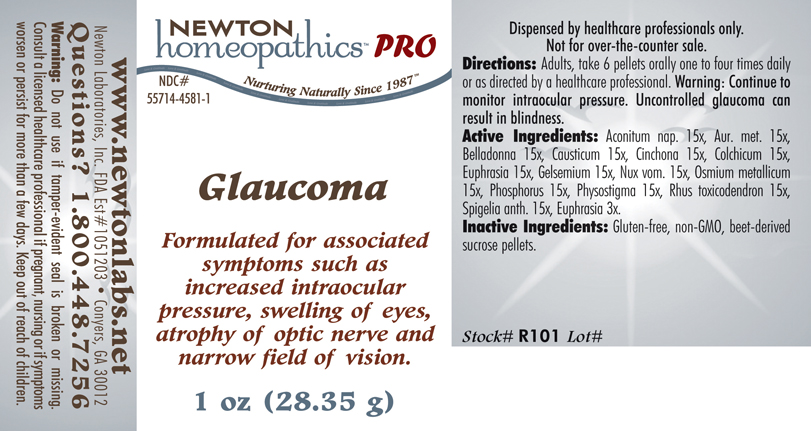 DRUG LABEL: Glaucoma 
NDC: 55714-4581 | Form: PELLET
Manufacturer: Newton Laboratories, Inc.
Category: homeopathic | Type: HUMAN PRESCRIPTION DRUG LABEL
Date: 20110601

ACTIVE INGREDIENTS: Aconitum Napellus 15 [hp_X]/1 g; Gold 15 [hp_X]/1 g; Atropa Belladonna 15 [hp_X]/1 g; Causticum 15 [hp_X]/1 g; Cinchona Officinalis Bark 15 [hp_X]/1 g; Colchicum Autumnale Bulb 15 [hp_X]/1 g; Euphrasia Stricta 15 [hp_X]/1 g; Gelsemium Sempervirens Root 15 [hp_X]/1 g; Strychnos Nux-vomica Seed 15 [hp_X]/1 g; Osmium 15 [hp_X]/1 g; Phosphorus 15 [hp_X]/1 g; Physostigma Venenosum Seed 15 [hp_X]/1 g; Toxicodendron Pubescens Leaf 15 [hp_X]/1 g; Spigelia Anthelmia 15 [hp_X]/1 g
INACTIVE INGREDIENTS: Sucrose

Glaucoma

INDICATIONS & USAGE SECTION

Glaucoma Formulated for associated symptoms such as increased intraocular pressure, swelling of eyes, atrophy of optic nerve and narrow field of vision.

DOSAGE & ADMINISTRATION SECTION

Directions: Adults, take 6 pellets orally one to four times daily or as directed by a healthcare professional. Warning: Continue to monitor intraocular pressure. Uncontrolled glaucoma can result in blindness.

ACTIVE INGREDIENT SECTION

Aconitum nap. 15x, Aur. met. 15x, Belladonna 15x, Causticum 15x, Cinchona 15x, Colchicum 15x, Euphrasia 15x, Gelsemium 15x, Nux vom. 15x, Osmium metallicum 15x, Phosphorus 15x, Physostigma 15x, Rhus toxicodendron 15x, Spigelia anth. 15x, Euphrasia 3x.

PURPOSE SECTION

Formulated for associated symptoms such as increased intraocular pressure, swelling of eyes, atrophy of optic nerve and narrow field of vision.

INACTIVE INGREDIENT SECTION

Inactive Ingredients: Gluten-free, non-GMO, beet-derived sucrose pellets.

QUESTIONS? SECTION

www.newtonlabs.net Newton Laboratories, Inc. FDA Est # 1051203 - Conyers, GA 30012
Questions? 1.800.448.7256

WARNINGS SECTION

Warning: Do not use if tamper - evident seal is broken or missing. Consult a licensed healthcare professional if pregnant, nursing or if symptoms worsen or persist for more than a few days. Keep out of reach of children.

PREGNANCY OR BREAST FEEDING SECTION

Consult a licensed healthcare professional if pregnant, nursing or if symptoms worsen or persist for more than a few days.

KEEP OUT OF REACH OF CHILDREN SECTION

Keep out of reach of children.